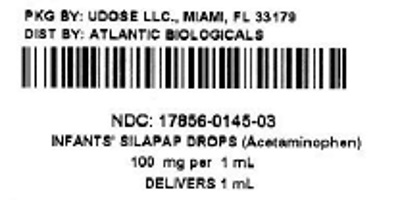 DRUG LABEL: Infants Silapap
                                    
NDC: 17856-0145 | Form: SOLUTION/ DROPS
Manufacturer: Atlantic Biologicals Corps
Category: otc | Type: HUMAN OTC DRUG LABEL
Date: 20160505

ACTIVE INGREDIENTS: Acetaminophen 80 mg/0.8 mL
INACTIVE INGREDIENTS: anhydrous citric acid; FD&C yellow no. 6; methylparaben; SACCHARIN SODIUM; sodium benzoate; sodium citrate; propylene glycol; water

Infant's Silapap Drops

Active Ingredient: Acetaminophen 80 mg (in each 0.8 mL)

Purpose: Fever reducer/pain reliever

Uses

temporarily:

■ reduces fever

■ relieves minor aches and pains due to: ■the common cold ■flu ■toothaches ■sore throat ■headaches

Warnings

This product contains acetaminophen. Severe liver damage may occur if your child takes: Liver warning:

- more than 5 doses in 24 hours, which is the maximum daily amount

- with other drugs containing acetaminophen

: if sore throat is severe, persists for more than 2 days, is accompanied or followed by fever, headache, rash, nausea, or vomiting, consult a doctor promptly. Sore throat warning

Do not use

- with any other product containing acetaminophen (prescription or nonprescription). If you are not sure whether a drug contains acetaminophen, ask a doctor or pharmacist.
- if your child is allergic to acetaminophen or any of the inactive ingredients in this product

liver disease. taking the blood thinning drug warfarin. Ask a doctor before use if your child has
Ask a doctor or pharmacist before use if your child is

When using this product

- do not exceed recommended dosage. (see overdose warning)

Stop use and ask a doctor if

■ new symptoms occur ■ redness or swelling is present ■ pain gets worse or lasts for more than 5 days ■ fever gets worse or lasts for more than 3 days.

These could be signs of serious condition.

. Keep out of reach of children

: Taking more than the recommended dose (overdose) may cause liver damage. In case of overdose, get medical help or contact a Poison Control Center right away, (1-800-222-1222). Quick medical attention is critical even if you do not notice any signs or symptoms. Overdose warning

Directions

■ ■ ■ find right dose on chart, if possible use weight to dose; otherwise, use age ■ use only enclosed dropper designed for use with this product, do not use any other dosing device ■ fill to dose level ■ dispense liquid slowly into child's mouth, toward inner cheek ■ may be given alone or mixed with formula, milk, juice etc. ■ If needed, repeat dose every 4 hours ■ do not give more than 5 times in 24 hours ■ Replace dropper tightly to maintain child resistance this product does not contain directions or complete warnings for adult use
do not give more than directed (see overdose warning)

Weight (lb) | Age (yr) | Dose (mL)
under 24 | under 2 years | ask a doctor
24-35 | 2-3 years | 1.6 mL (0.8 + 0.8 mL)

For accurate dosing follow dosing instructions using the enclosed dropper. Fill dropper to 0.8 mL or prescribed level, and dispense with a single firm squeeze of the dropper bulb. Store between 20° - 25°C (68° - 77°F)
Other information

Inactive ingredients

citric acid, FD&C yellow no. 6, cherry flavor, methylparaben, saccharin sodium, sodium benzoate, sodium citrate, propylene glycol and purified water.

Comments

1-888-974-5279

Manufactured by:

Silarx Pharmaceuticals, Inc. 1033 Stoneleigh Ave. Carmel , NY 10512